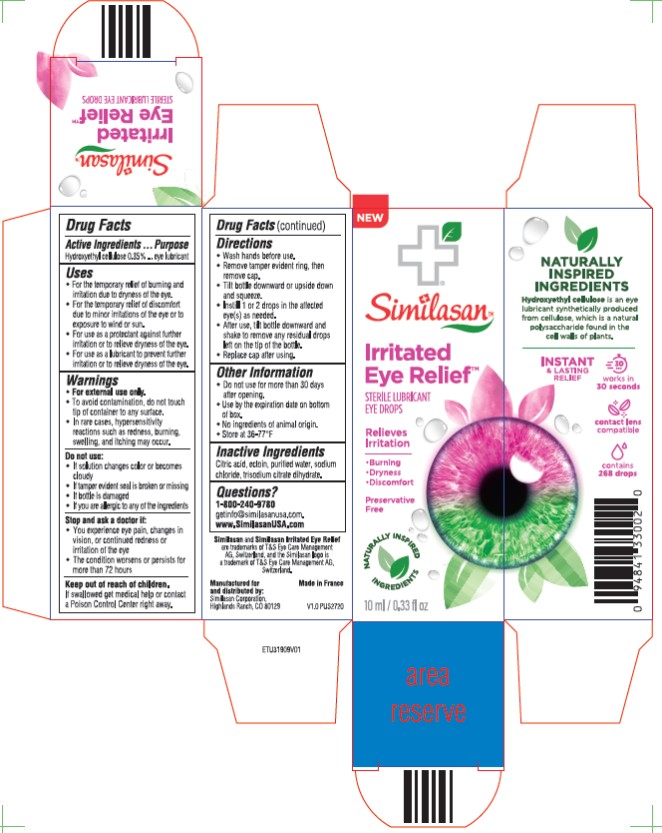 DRUG LABEL: Naturally Inspired Irritated Eye Relief
NDC: 59262-801 | Form: SOLUTION/ DROPS
Manufacturer: Similasan Corporation
Category: otc | Type: HUMAN OTC DRUG LABEL
Date: 20251028

ACTIVE INGREDIENTS: HYDROXYETHYL CELLULOSE, UNSPECIFIED 0.35 mg/1 mL
INACTIVE INGREDIENTS: CITRIC ACID; ECTOIN; WATER; SODIUM CHLORIDE; TRISODIUM CITRATE DIHYDRATE

Naturally Inspired Irritated Eye Relief

Active Ingredient

Hydroxyethyl cellulose 0.35%

Purpose

Eye lubricant

Uses

- For the temporary relief of burning and irritation due to dryness of the eye
- For the temporary relief of discomfort due to minor irritations of the eye or to exposure to wind and sun
- For use as a protectant against further irritation or to relieve dryness of the eye
- For use as a lubricant to prevent further irritation or to relieve dryness of the eye.

Warnings

- For external use only
- To avoid contamination, do not touch the tip of container to any surface.
- In rare cases, hypersensitivity reactions such as redness, burning, swelling, and itching may occur.

Do not use:

- If solution changes color or becomes cloudy
- If tamper evident seal is broken or missing
- If bottle is damaged
- If you are allergic to any of the ingredients

Stop and ask a doctor if:

- You experience eye pain, changes in vision, or continued redness or irritation of the eye
- The condition worsens or persists for more than 72 hours

Keep out of reach of children.

- If swallowed, get medical help or contact a Poison Control Center right away.

Directions

- Wash hands well before use.
- Remove tamper evident ring, then remove cap.
- Tilt bottle downward or upside down and squeeze.
- Instill 1 or 2 drops in the affected eye(s) as needed.
- After use, tilt bottle downward and shake to remove any residual drops left on the tip of the bottle.
- Replace cap after using.

Other Information

- Do not use for more than 30 days after opening.
- Use by the expiration date on bottom of the box.
- No ingredients of animal origin.
- Store at 36-77°F

Inactive Ingredients

Citric acid, ectoin, purified water, sodium chloride, trisodium citrate dihydrate

Questions?

1-800-240-9780

getinfo@similasanusa.com

www.similasanUSA.com

Principle Display Panel

Similasan

Irritated Eye Relief
Sterile Lubricant Eye Drops
0.33 FL OZ (10 ml)